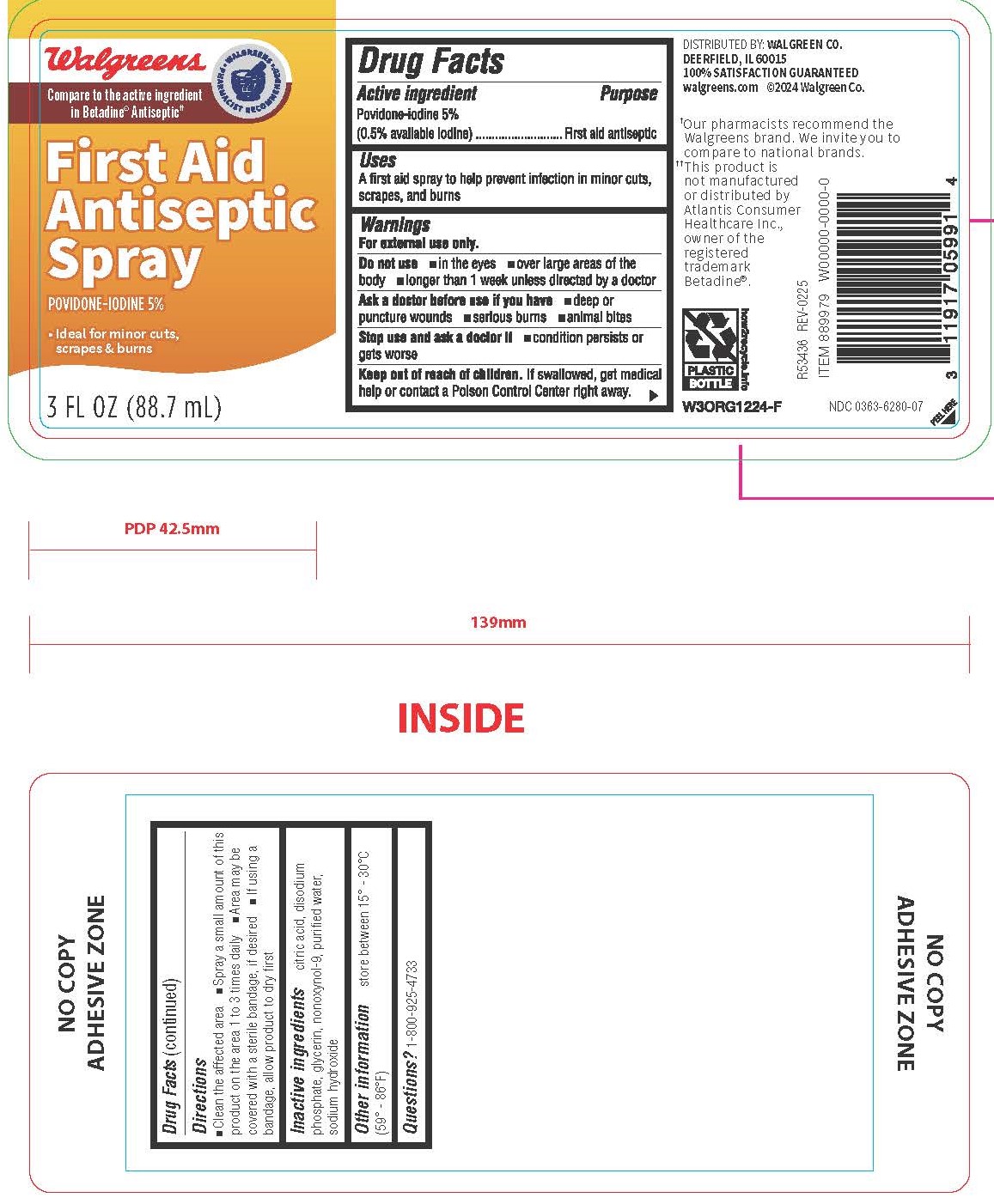 DRUG LABEL: First Aid Antiseptic
NDC: 0363-6280 | Form: SPRAY
Manufacturer: Walgreen Company
Category: otc | Type: HUMAN OTC DRUG LABEL
Date: 20251022

ACTIVE INGREDIENTS: POVIDONE-IODINE 5 mg/1 mL
INACTIVE INGREDIENTS: ANHYDROUS CITRIC ACID; WATER; DISODIUM PHOSPHATE; NONOXYNOL-9; GLYCERIN; SODIUM HYDROXIDE

6280 - Walgreen

Drug Facts

Active ingredient

Povidone-iodine 5% (0.5% available iodine)

Purpose

First aid antiseptic

Uses

A first aid spray to hel prevent infection in minor cuts, scrapes and burns

WARNINGS

For external use only.

Do not use

- in the eyes
- over large areas of the body
- longer than 1 week unless directed by a doctor

Ask a doctor before use if you have

- deep or puncture wounds
- serious burns
- animal bites

Stop use and ask a doctor if

condition persists or gets worse

Keep out of reach of children. If swallowed, get medical help or contact a Poison Control Center right away.

Directions

- Clean the affected area
- Spray a small amount of this product on the area 1 to 3 times daily
- Area may be covered with a sterile bandage, if desired
- If using a bandage, allow product to dry first

INACTIVE INGREDIENT

citric acid, disodium phosphate, glycerin, nonoxynol-9, purified water, sodium hydroxide

Other information

store between 15° - 30°C (59° - 86°F)

QUESTIONS

1-800-925-4733

STATEMENT OF IDENTITY

DISTRIBUTED BY: WALGREEN CO. DEERFIELD, IL 60015 100% SATISFACTION GUARANTEED walgreens.com ©2024 Walgreen Co.

†Our pharmacists recommend the Walgreens brand. We invite you to compare to national brands.

††This product is not manufactured or distributed by Atlantis Consumer Healthcare Inc., owner of the registered trademark Betadine®

PACKAGE LABEL

Walgreens

Compare to the active ingredient in Betadine® Antiseptic

First Aid Antispetic Spray

Povidone-Iodine 5%

Ideal for minor cuts, scrapes & burns

3 Fl OZ (88.7 mL)